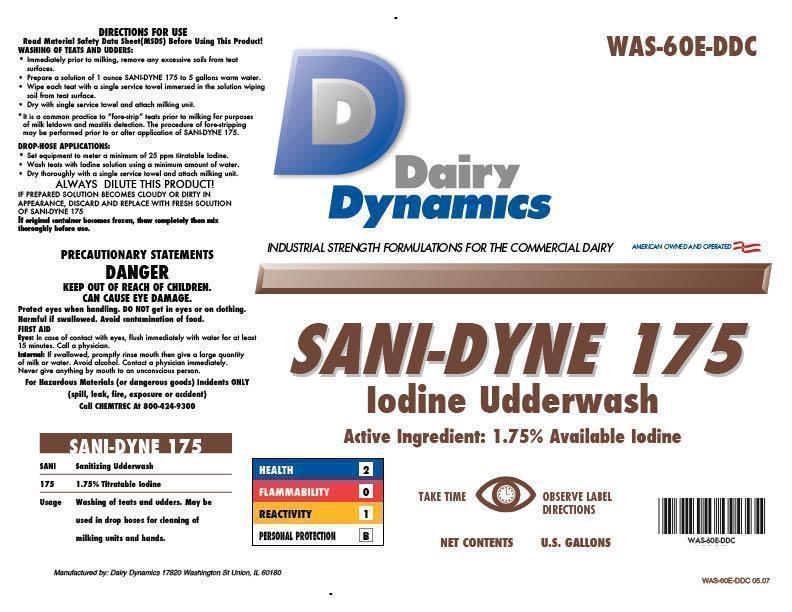 DRUG LABEL: SANI-DYNE 175
NDC: 67351-600 | Form: SOLUTION, CONCENTRATE
Manufacturer: Dairy Dynamics L.L.C.
Category: animal | Type: OTC ANIMAL DRUG LABEL
Date: 20141202

ACTIVE INGREDIENTS: IODINE 17.5 g/1 L

SANI-DYNE 175

VETERINARY INDICATIONS

Iodine Udderwash

1.75% Available Iodine

Usage Washing of teats and udders. May be used in drop hoses for cleaning of milking units and hands.

DIRECTION FOR USE

WASHING OF TEATS AND UDDERS:

- Immediately prior to milking, remove any excessive soils from teat surfaces.
- Prepare a solution of 1 ounce SANI-DYNE 175 to 5 gallons warm water.
- Wipe each teat with a single service towel immersed in the solution wiping soil from teat surface.
- Dry with a single service town and attach milking unit.

*It is common practice to “fore-strip” teats prior to milking for purposes of milk letdown and mastitis detection. The procedure for fore-stripping may be performed prior to or after application of SANI-DYNE 175.

DROP-HOSE APPLICATIONS:

- Set equipment to meter a minimum of 25 ppm titratable Iodine.
- Wash teats with Iodine solution using a minimum amount of water.
- Dry thoroughly with a single service towel and attach milking unit.

ALWAYS DILUTE THIS PRODUCT!

IF PREPARED SOLUTION BECOME CLOUDY OR DIRTY IN APPEARANCE, DISCARD AND REPLACE WITH FRESH SOLUTION OF SANI-DYNE 175.

If original container becomes frozen, thaw completely then mix thoroughly before use.

WARNINGS AND PRECAUTIONS

PRECUATIONARY STATEMENTS

DANGER

KEEP OUT OF REACH OF CHILDREN.

CAN CAUSE EYE DAMAGE.

Protect eyes when handling. DO NOT get in eyes or on clothing.

Harmful if swallowed. Avoid contamination of food.

FIRST AID

Eyes: In case of contact with eyes, flush immediately with water for at least 15 minutes. Call a physician.

Internal: If swallowed, promptly rinse mouth then give a large quantity of milk or water. Avoid alcohol. Contact a physician immediately. Never give anything by mouth to an unconscious person.

For Hazardous Materials (or dangerous goods) Incidents ONLY (spill, leak, fire, exposure or accident)

Call CHEMTREC At 800-424-9300

HEALTH - 2

FLAMMABILITY - 0

REACTIVITY - 1

PERSONAL PROTECTION - B

ACTIVE INGREDIENT

Dairy Dynamics

INDUSTRIAL STRENGTH FORMULATIONS FOR THE COMMERCIAL DAIRY

AMERICAN OWNED AND OPERATED

SANI-DYNE 175

Iodine Udderwash

Active Ingredient: 1.75% Available Iodine

TAKE TIME OBSERVE LABEL DIRECTIONS

NET CONTENTS U.S. GALLONS